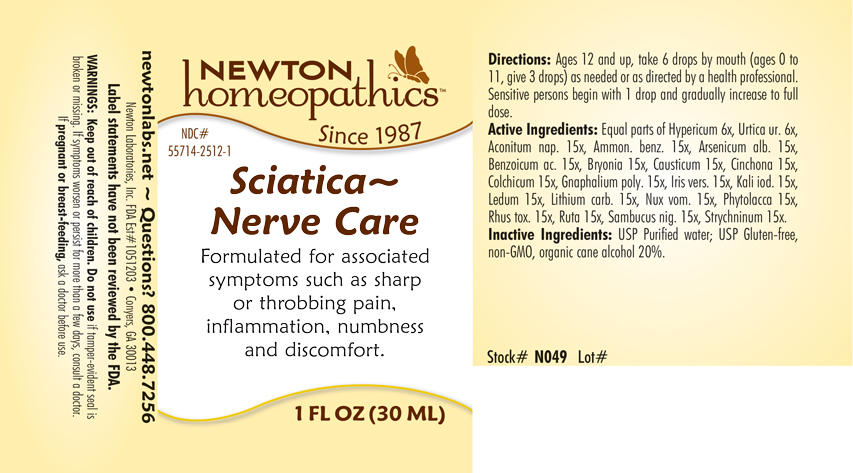 DRUG LABEL: Sciatica-Nerve Care
NDC: 55714-2512 | Form: LIQUID
Manufacturer: Newton Laboratories, Inc.
Category: homeopathic | Type: HUMAN OTC DRUG LABEL
Date: 20250210

ACTIVE INGREDIENTS: ACONITUM NAPELLUS 15 [hp_X]/1 mL; AMMONIUM BENZOATE 15 [hp_X]/1 mL; ARSENIC TRIOXIDE 15 [hp_X]/1 mL; BENZOIC ACID 15 [hp_X]/1 mL; BRYONIA ALBA ROOT 15 [hp_X]/1 mL; CAUSTICUM 15 [hp_X]/1 mL; CINCHONA OFFICINALIS BARK 15 [hp_X]/1 mL; COLCHICUM AUTUMNALE BULB 15 [hp_X]/1 mL; PSEUDOGNAPHALIUM OBTUSIFOLIUM 15 [hp_X]/1 mL; IRIS VERSICOLOR ROOT 15 [hp_X]/1 mL; POTASSIUM IODIDE 15 [hp_X]/1 mL; RHODODENDRON TOMENTOSUM LEAFY TWIG 15 [hp_X]/1 mL; LITHIUM CARBONATE 15 [hp_X]/1 mL; STRYCHNOS NUX-VOMICA SEED 15 [hp_X]/1 mL; PHYTOLACCA AMERICANA ROOT 15 [hp_X]/1 mL; TOXICODENDRON PUBESCENS LEAF 15 [hp_X]/1 mL; RUTA GRAVEOLENS FLOWERING TOP 15 [hp_X]/1 mL; SAMBUCUS NIGRA FLOWERING TOP 15 [hp_X]/1 mL; STRYCHNINE 15 [hp_X]/1 mL; HYPERICUM PERFORATUM 6 [hp_X]/1 mL; URTICA URENS 6 [hp_X]/1 mL
INACTIVE INGREDIENTS: WATER; ALCOHOL

Sciatica 2512L

INDICATIONS & USAGE SECTION

Formulated for associated symptoms such as sharp or throbbing pain, Inflammation, numbness and discomfort.

DOSAGE & ADMINISTRATION SECTION

Directions: Ages 12 and up, take 6 drops by mouth (ages 0 to 11, give 3 drops) as needed or as directed by a health professional. Sensitive persons begin with 1 drop and gradually increase to full dose.

OTC - ACTIVE INGREDIENT SECTION

Equal parts of Hypericum perforatum 6x, Urtica urens 6x, Aconitum napellus 15x, Ammonium benzoicum 15x, Arsenicum album 15x, Benzoicum acidum 15x, Bryonia 15x, Causticum 15x, Cinchona officinalis 15x, Colchicum autumnale 15x, Gnaphalium polycephalum 15x, Iris versicolor 15x, Kali iodatum 15x, Ledum palustre 15x, Lithium carbonicum 15x, Nux vomica 15x, Phytolacca decandra 15x, Rhus toxicodendron 15x, Ruta graveolens 15x, Sambucus nigra 15x, Strychninum 15x.

OTC - PURPOSE SECTION

Formulated for associated symptoms such as sharp or throbbing pain, Inflammation, numbness and discomfort.

INACTIVE INGREDIENT SECTION

Inactive Ingredients: USP Purified Water; USP Gluten-free, non-GMO, organic cane alcohol 20%.

QUESTIONS SECTION

newtonlabs.net – Questions? 800.448.7256

Newton Laboratories, Inc. FDA Est # 1051203 - Conyers, GA 30013

WARNINGS SECTION

WARNINGS: Keep out of reach of children. Do not use if tamper-evident seal is broken or missing. If symptoms worsen or persist for more than a few days, consult a doctor. If pregnant or breast-feeding, ask a doctor before use.

OTC - PREGNANCY OR BREAST FEEDING SECTION

If pregnant or breast-feeding, ask a doctor before use.

OTC - KEEP OUT OF REACH OF CHILDREN SECTION

Keep out of reach of children.